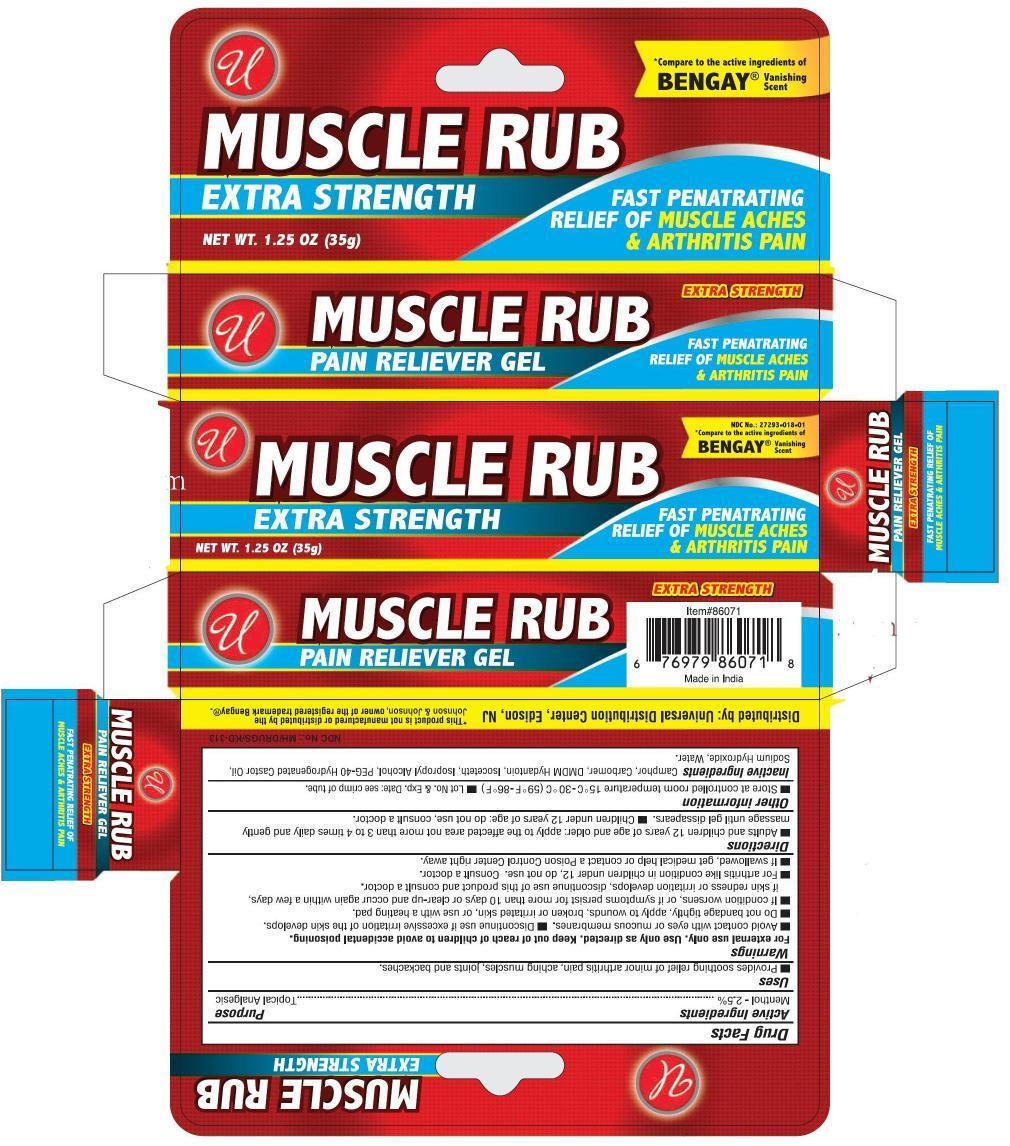 DRUG LABEL: Muscle Rub
NDC: 52000-020 | Form: GEL
Manufacturer: Universal Distribution Center LLC
Category: otc | Type: HUMAN OTC DRUG LABEL
Date: 20241205

ACTIVE INGREDIENTS: MENTHOL, UNSPECIFIED FORM 0.025 g/1 g
INACTIVE INGREDIENTS: CAMPHOR (SYNTHETIC); CARBOMER HOMOPOLYMER TYPE C (ALLYL PENTAERYTHRITOL CROSSLINKED); DMDM HYDANTOIN; ISOCETETH-20; ISOPROPYL ALCOHOL; POLYOXYL 40 HYDROGENATED CASTOR OIL; SODIUM HYDROXIDE; WATER

U Muscle Rub Gel

Active Ingredient

Menthol 2.5%

Purpose

Topical Analgesic

Uses

- Provides soothing relief of minor arthritis pain, aching muscles, joints and backaches.

Warnings

For external use only. Use only as directed. Keep out of reach of children to avoid accidental poisoning.

- Avoid contact with eyes or mucous membranes.
- Discontinue use if excessive irritation of the skin develops.
- Do not bandage tightly, apply to wounds, broken or irritated skin, or use with a heating pad.
- If condition worsens, or if symptoms persist for more than 10 days or clear-up and occur again within a few days, if skin redness or irritation develops, discontinue use of this product and consult a doctor.
- For arthritis like conditions in children under 12, do not use. Consult a doctor.

KEEP OUT OF REACH OF CHILDREN

- If swallowed, get medical help or contact a Poison Control Center right away.

Directions

- Adults and children 12 years of age and older: apply to affected area not more than 3 to 4 times daily and gently massage until gel disappears.
- Children under 12 years of age: do not use, consult a doctor

Other Information

- Store at controlled room temperature 15°C to 30°C (59°F to 86°F)
- Lot No. & Exp. Date: see crimp of tube.

Inactive Ingredients

Camphor, Carbomer, DMDM Hydantoin, Isoceteth, Isopropyl Alcohol, PEG-40 Hydrogenated Castor Oil, Sodium Hydroxide, Water

PACKAGE LABEL

PRINCIPAL DISPLAY PANEL

MUSCLE RUB GEL

NET WT 1.25 OZ (35 g)